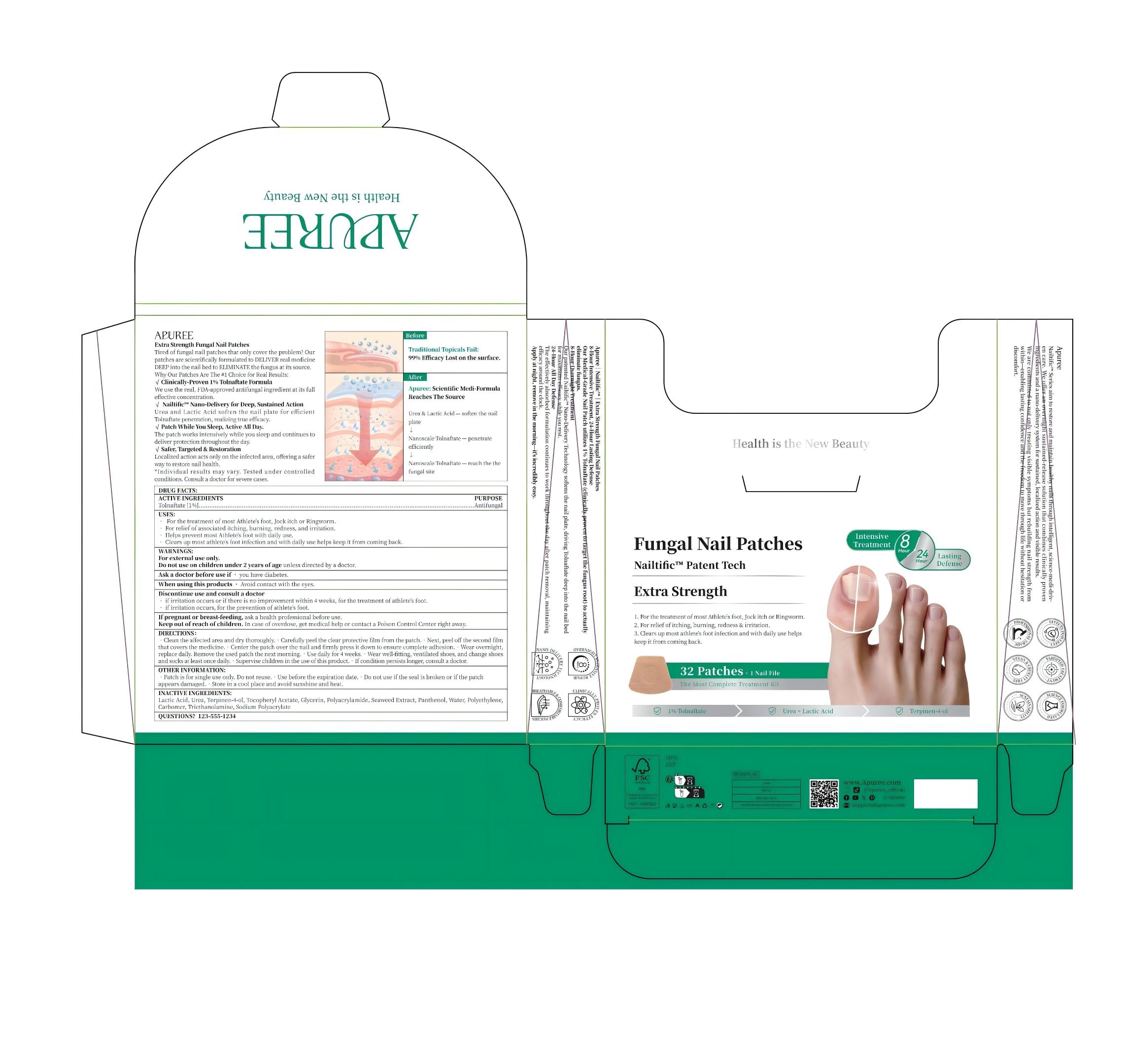 DRUG LABEL: APUREE  Pure Nailtific  Extra-Strength Fungal Nail Patches
NDC: 84167-332 | Form: PATCH
Manufacturer: Guangzhou Meixi Biotechnology Co., Ltd.
Category: otc | Type: HUMAN OTC DRUG LABEL
Date: 20251124

ACTIVE INGREDIENTS: TOLNAFTATE 1 g/1 1
INACTIVE INGREDIENTS: WATER; PANTHENOL; TRIETHANOLAMINE; TERPINEN 4-PROPIONATE; LACTIC ACID; POLYETHYLENE; (4-(TRIFLUOROMETHOXY)PHENYL)UREA; CARBOMER; POLYACRYLAMIDE (10000 MW); GLYCERIN; SODIUM POLYACRYLATE (8000 MW)

ACTIVE INGREDIENT

Tolnaftate

INACTIVE INGREDIENT

Water,Glycerol/Glycerin,Polyethylene,Carbomer,Triethanolamine,Sodium Polyacrylate,Polyacrylamide,Urea,Urea,Seaweed Extract,Panthenol,Tocopheryl Acetate

DOSAGE AND ADMINISTRATION

32 Patches+1 Nail File

keep out of reach of children

keep out of reach of children

INDICATIONS AND USAGE

PUREE Pure Nailtific Extra-Strength Fungal Nail Patches

PURPOSE

PUREE Pure Nailtific Extra-Strength Fungal Nail Patches